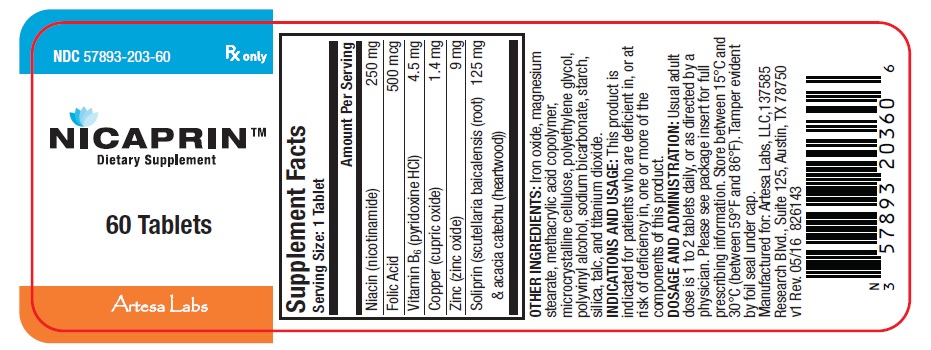 DRUG LABEL: NICAPRIN
NDC: 57893-203 | Form: TABLET
Manufacturer: Artesa Labs, LLC
Category: other | Type: DIETARY SUPPLEMENT
Date: 20160923

ACTIVE INGREDIENTS: NIACIN 250 mg/1 1; FOLIC ACID 500 ug/1 1; CUPRIC OXIDE 1.4 mg/1 1; ZINC OXIDE 9 mg/1 1; PYRIDOXINE HYDROCHLORIDE 4.5 mg/1 1
INACTIVE INGREDIENTS: FERRIC OXIDE RED; MAGNESIUM STEARATE; METHACRYLIC ACID - ETHYL ACRYLATE COPOLYMER (1:1) TYPE A; MICROCRYSTALLINE CELLULOSE; POLYETHYLENE GLYCOL, UNSPECIFIED; POLYVINYL ALCOHOL, UNSPECIFIED; SODIUM BICARBONATE; STARCH, CORN; SILICON DIOXIDE; TALC; TITANIUM DIOXIDE; SCUTELLARIA BARBATA WHOLE; ACACIA CATECHU WOOD

NICAPRINTM

HEALTH CLAIM

Rx Only Dietary Supplement

DESCRIPTION:

This product is a prescription dietary supplement for oral administration, specifically formulated for the dietary management of patients with unique nutritional needs who require increased levels of one or more of the ingredients in this product. Each tan colored caplet-shaped tablet is debossed with “203” on one side and plain on the other.

INGREDIENTS:

Each tablet of NicaprinTM contains:

Niacin (nicotinamide) | 250 mg
Folic Acid | 500 mcg
Vitamin B6 (pyridoxine HCl) | 4.5 mg
Copper (cupric oxide) | 1.4 mg
Zinc (zinc oxide) | 9 mg
Soliprin (scutellaria baicalensis (root) & acacia catechu (heartwood)) | 125 mg

OTHER INGREDIENTS:

Iron oxide, magnesium stearate, methacrylic acid copolymer, microcrystalline cellulose, polyethylene glycol, polyvinyl alcohol, sodium bicarbonate, starch, silica, talc, and titanium dioxide.

INDICATIONS AND USAGE:

This product is indicated for patients who are deficient in, or at risk of deficiency in, one or more of the components of this product.

CONTRAINDICATIONS

This product is contraindicated in patients with known hypersensitivity to any of the ingredients.

WARNINGS AND PRECAUTIONS:

This product should be administered with caution in patients with a history of liver disease, jaundice or diabetes mellitus. While prescribing this product for pregnant women, nursing mothers, or for women prior to conception, their medical condition and use of other drugs, herbs and/or supplements should be considered. Folic acid above 1 mg daily may obscure pernicious anemia in that hematologic remission may occur while neurological manifestations remain progressive. Abnormal liver functions tests have been reported in persons taking daily doses of 500 mg or more of niacinamide.

KEEP THIS AND ALL MEDICATION OUT OF THE REACH OF CHILDREN.

PREGNANCY & NURSING MOTHERS:

This product is not indicated for use as a prenatal/postnatal multivitamin for lactating and nonlactating mothers. Physicians and medical practitioners should administer this product with caution to patients who are pregnant, lactating and/or taking medication.

ADVERSE REACTIONS:

Allergic sensitization has been reported following both oral and parenteral administration of folic acid. You should call your doctor for medical advice about side effects. To report a serious adverse event, call 1-855-899-4237.

DOSAGE AND ADMINISTRATION:

Usual adult dose is 1 to 2 tablets daily, or as directed by a physician.

HOW SUPPLIED:

This product is supplied in the following size(s):
60 count bottles, NDC 57893-203-60

HEALTH CLAIM

Store between 15°C and 30°C (between 59°F and 86°F). Tamper evident by foil seal under cap.

HEALTH CLAIM

Manufactured for:
Artesa Labs, LLC
137585 Research Blvd.
Suite 125
Austin, TX 78750
v1 Rev. 05/16 826146

PRINCIPAL DISPLAY PANEL - 60 TABLET BOTTLE LABEL

NDC 57893-203-60

Rx Only

NICAPRINTM

Dietary Supplement

60 Tablets

Artesa Labs